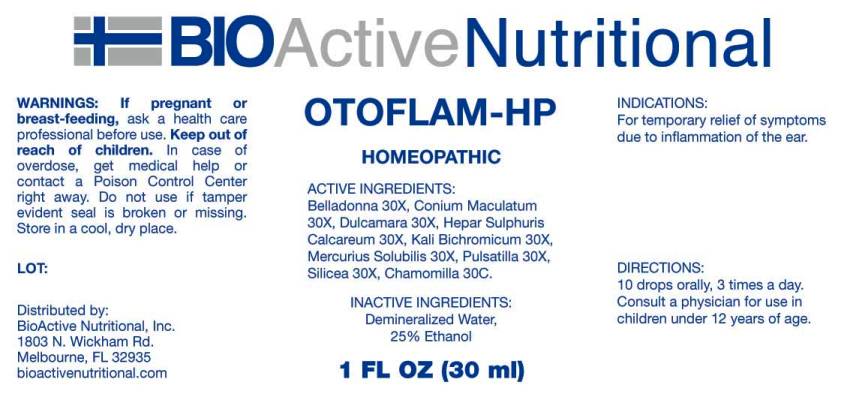 DRUG LABEL: Otoflam
NDC: 43857-0034 | Form: LIQUID
Manufacturer: BioActive Nutritional, Inc.
Category: homeopathic | Type: HUMAN OTC DRUG LABEL
Date: 20170404

ACTIVE INGREDIENTS: ATROPA BELLADONNA 30 [hp_X]/1 mL; CONIUM MACULATUM FLOWERING TOP 30 [hp_X]/1 mL; SOLANUM DULCAMARA TOP 30 [hp_X]/1 mL; CALCIUM SULFIDE 30 [hp_X]/1 mL; POTASSIUM DICHROMATE 30 [hp_X]/1 mL; MERCURIUS SOLUBILIS 30 [hp_X]/1 mL; PULSATILLA VULGARIS 30 [hp_X]/1 mL; SILICON DIOXIDE 30 [hp_X]/1 mL; MATRICARIA RECUTITA 30 [hp_C]/1 mL
INACTIVE INGREDIENTS: ALCOHOL; WATER

Drug Facts:

ACTIVE INGREDIENTS:

Belladonna 30X, Conium Maculatum 30X, Dulcamara 30X, Hepar Sulphuris Calcareum 30X, Kali Bichromicum 30X, Mercurius Solubilis 30X, Pulsatilla 30X, Silicea 30X, Chamomilla 30C.

INDICATIONS:

For temporary relief of symptoms due to inflammation of the ear.

WARNINGS:

If pregnant or breast-feeding, ask a health care professional before use.

Keep out of reach of children. In case of overdose, get medical help or contact a Poison Control Center right away.

Do not use if tamper evident seal is broken or missing.

Store in a cool, dry place.

KEEP OUT OF REACH OF CHILDREN:

10 drops orally, 3 times a day. Consult a physician for use in children under 12 years of age.

DIRECTIONS:

10 drops orally, 3 times a day. Consult a physician for use in children under 12 years of age.

INDICATIONS:

For temporary relief of symptoms due to inflammation of the ear.

INACTIVE INGREDIENTS:

Demineralized Water, 25% Ethanol.

QUESTIONS:

Distributed by:
BioActive Nutritional, Inc.
1803 N. Wickham Rd.
Melbourne, FL 32935
bioactivenutritional.com

PACKAGE LABEL DISPLAY:

BIOActive Nutritional

OTOFLAM HP

HOMEOPATIC

1 FL OZ (30 ml)